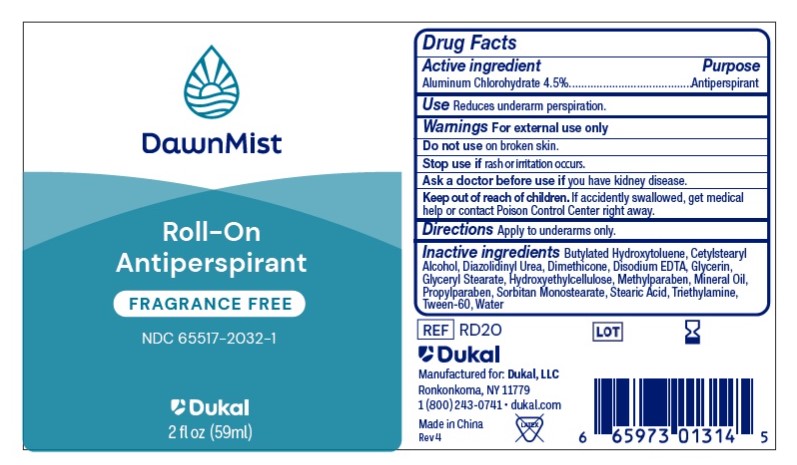 DRUG LABEL: DawnMist Antiperspirant
NDC: 65517-2032 | Form: LOTION
Manufacturer: Dukal LLC
Category: otc | Type: HUMAN OTC DRUG LABEL
Date: 20250102

ACTIVE INGREDIENTS: ALUMINUM CHLOROHYDRATE 45 mg/1 mL
INACTIVE INGREDIENTS: METHYLPARABEN; PROPYLPARABEN; SORBITAN MONOSTEARATE; MINERAL OIL; EDETATE DISODIUM; POLYSORBATE 60; GLYCERIN; HYDROXYETHYL CELLULOSE, UNSPECIFIED; WATER; BUTYLATED HYDROXYTOLUENE; TRIETHYLAMINE; STEARIC ACID; CETOSTEARYL ALCOHOL; DIMETHICONE; DIAZOLIDINYL UREA; GLYCERYL MONOSTEARATE

DawnMist Roll-On Antiperspirant 4.5% - Fragrance Free

Active Ingredient

Aluminum Chlorohydrate 4.5%

Purpose

Antiperspirant

Use

Reduces underarm perspiration

Warnings

For external use only.

Do not use on broken skin

Ask a doctor before use if you have kidney disease.

Keep out of reach of children. If accidently swallowed, get medical help or contact Poison Control Center right away.

Directions

Apply to underarms only.

Inactive ingredients

Butylated Hydroxytoluene, Cetylstearyl Alcohol, Diazolidinyl Urea, Dimethicone, Disodium EDTA, Glycerin, Glyceryl stearate, Hydroxyethylcellulose, Methylparaben, Mineral Oil, Propylparaben, Sorbitan Monostearate, Stearic acid, Triethylamine, Tween-60, Water

Principal Display Panel

DawnMist

Roll-On

Antiperspirant

Fragrance Free

NDC 65517-2032-1

Dukal

2FL.OZ. (59ml)